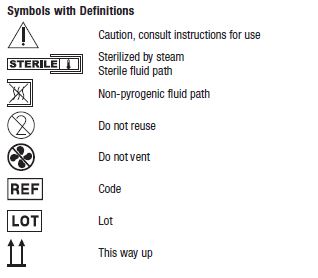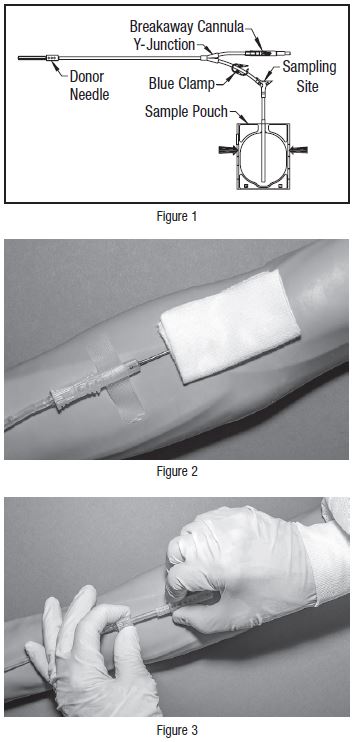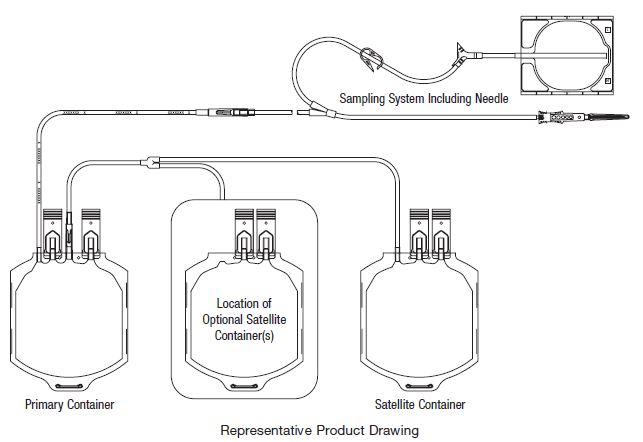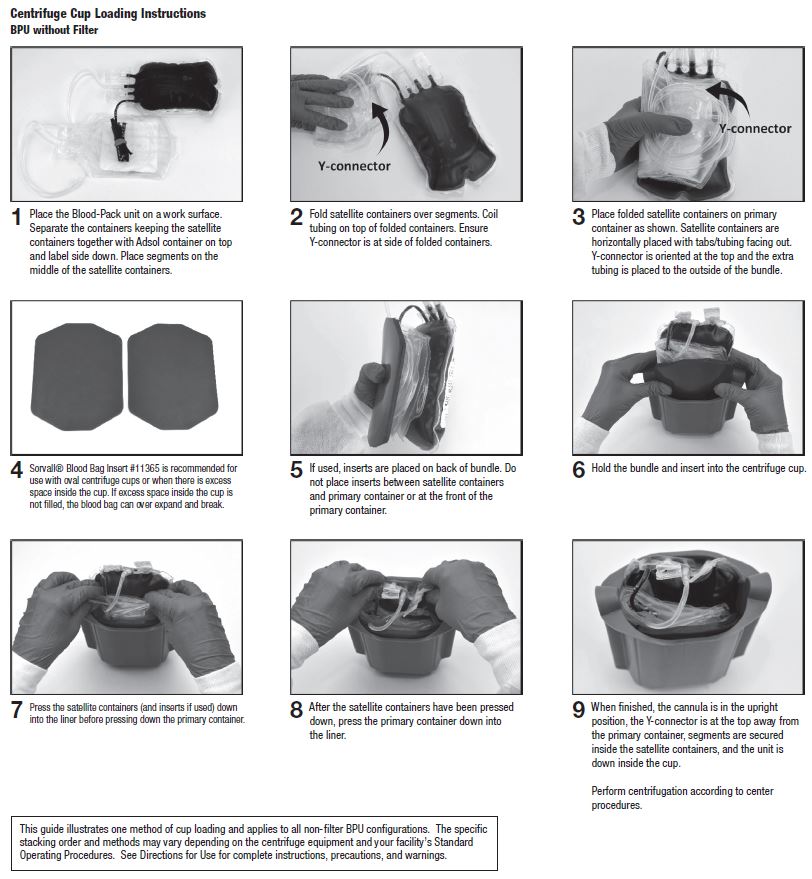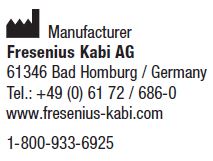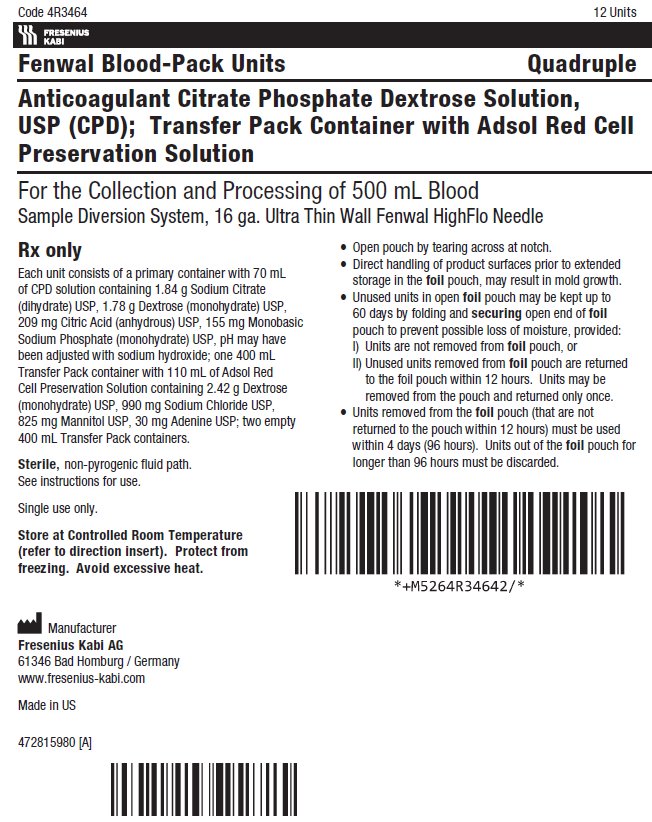 DRUG LABEL: ADSOL Red Cell Preservation Solution System in Plastic Container (PL 146 Plastic)
NDC: 0942-6459 | Form: KIT | Route: INTRAVENOUS
Manufacturer: Fenwal, Inc.
Category: prescription | Type: HUMAN PRESCRIPTION DRUG LABEL
Date: 20221102

ACTIVE INGREDIENTS: Trisodium Citrate Dihydrate 1.84 g/70 mL; Dextrose Monohydrate 1.78 g/70 mL; Anhydrous Citric Acid 209 mg/70 mL; Sodium Phosphate, Monobasic, Monohydrate 155 mg/70 mL; Dextrose Monohydrate 2.42 g/110 mL; Sodium Chloride 990 mg/110 mL; Mannitol 825 mg/110 mL; Adenine 30 mg/110 mL
INACTIVE INGREDIENTS: Sodium Hydroxide; Water; Water

4R3440, 4R3468, 4R3464 Fresenius Kabi Fenwal Blood-Pack Units Rx only Using Anticoagulant Citrate Phosphate Dextrose Solution, USP (CPD) with an Integrally Attached Container of Adsol Red Cell Preservation Solution and Fenwal HighFlo Needle

Contains Sample Diversion System for the collection of whole blood samples for laboratory testing.

Instructions for Use

Collection Procedure:

Use aseptic technique.

Notes:

• If Sample Diversion System is not used, donor samples may be collected using an alternate method following standard procedures.
• Nominal tubing dimensions of product are 0.118" inner diameter x 0.025" wall thickness.

Precautions:

• Upon removal of Blood-Pack unit from the clear plastic overwrap, visually inspect the unit.
• Do not use the product if the in-line cannula is broken and/or anticoagulant is present in the sample pouch or in the tubing from the in-line cannula to the sample pouch and donor needle (see Figure 1). Note that condensation in the empty tubing of the Blood-Pack unit is expected as a result of the sterilization process.
• Do not use unless the solutions are clear.

1. Identify Blood-Pack unit using appropriate donor identification system.

2. Donor Scale

• Adjust donor scale to desired collection weight.
• Position primary container on the donor scale as far as possible below donor arm.

3. Clamp donor tubing between the HighFlo1 needle and primary container with clamp. (This step can be performed prior to step 1 or 2.)

4. Visually inspect the tubing from the in-line cannula to the sample pouch and donor needle, as well as the sample pouch to reconfirm that there is no anticoagulant present.

Note: Ensure that the sample pouch remains below the donor’s arm.

5. Following blood center procedures, apply pressure to donor’s arm and disinfect site of

venipuncture.

6. Remove needle cover per instructions below:

• Holding the hub and cover near the tamper-evident seal, twist cover and hub in opposite directions to break seal.
• Remove needle cover, being careful not to drag the cover across the needle point.

7. Following blood center procedures, perform venipuncture, appropriately secure donor needle and/or tubing and release hemostat.

8. When good blood flow is established, stabilize the front of the needle guard to arm with tape (see Figure 2).

9. Allow the sample pouch to fill with blood according to center procedure. Monitor blood flow into sample pouch.

Notes:

• The sample pouch contains an average fill volume of approximately 53 mL with a maximum fill volume of approximately 60 mL when filled to capacity.
• If less blood sample volume is required, the flow to the sample pouch may be stopped prior to completely filling the pouch. For example, in order to target a fill volume of approximately 40 mL, fill to the level indicated by the arrows in Figure 1. Ensure the pouch is hanging vertically.
• The tube leading from the Y-junction to the sample pouch contains an additional volume of approximately 2 mL.

Precautions:

• Do not elevate or squeeze the sample pouch as this could cause blood to backflow from the sample pouch into the collection system.
• Once the sample pouch is filled to desired volume, complete steps 10 – 18 within approximately 4 minutes to avoid possible clot formation in the tubing and/or sample pouch.

10. Close the blue clamp on tubing between the Y-junction and the sample pouch.

11. Break the in-line cannula below the Y-junction in the donor tubing to the primary container allowing blood collection to proceed. To completely break the in-line cannula, grasp with both hands. Snap it at a 90° angle in one direction, and then bend it at a 90° angle in the opposite direction. Ensure the in-line cannula is completely broken and that the blood flows freely to the primary container.

Precaution: Failure to break the in-line cannula completely may result in restricted blood flow.

12. Following blood center procedures, mix blood and anticoagulant in the primary container immediately and at several intervals during collection.

13. Following blood center procedures, hermetically seal the tubing between the sampling site and the Y-junction to maintain sterility of the blood collection system prior to removing blood samples.

Warning:

• Do not proceed with the remaining steps until the tubing leading to the sample pouch is hermetically sealed between the sampling site and the Y-junction. To maintain the whole blood collection container as a closed system, the tubing between the sample pouch and Y-junction must be hermetically sealed prior to inserting the access device into the sampling site. Failure to do so may lead to contamination of the whole blood collection.

14. Insert the access device by pushing firmly into the sampling site until the membrane seal is penetrated.

Note: If the access device is assembled such that the outer barrel is screwed onto the Luer, make sure to rotate clockwise upon insertion to avoid barrel detaching from Luer.

15. Open the cap on the access device (if applicable). Hold access device so that the

sample pouch hangs down.

16. Directly align the vacuum sample tube with the internal needle in the access device. Insert vacuum sample tube into device.

17. Allow vacuum sample tube to fill with blood then remove from the access device.

18. Repeat steps 16 and 17 until the desired number of vacuum sample tubes have been filled.

Notes:

• If the access device needs to be replaced, clamp the tubing between the sampling site and the sample pouch. Then, grasp base of sampling site with one hand and pull the access device out with the other hand. Firmly insert the new access device. Remove clamp and continue sampling.
• If the access device is assembled such that the outer barrel is screwed onto the Luer, make sure to rotate clockwise upon removal to avoid barrel detaching from Luer.
• The access device can only be replaced one time.

Precaution: When replacing access device, be careful to avoid contact with any blood droplets on the Luer or sampling site. Discard used access device appropriately.

19. Collect the appropriate volume based on Blood-Pack unit used.

Note: The volume of anticoagulant is sufficient for the blood collection indicated on Blood-Pack unit ± 10%.

Precaution: Once the desired blood volume is collected, complete steps 20-23 within approximately 4 minutes to avoid possible clot formation in the tubing.

20. Release pressure on the donor’s arm. If appropriate, apply clamp to donor tubing

between the needle and the Y-junction.

21. Hermetically seal donor tubing near in-line cannula on side leading to the primary

container.

22. Withdrawal of Needle (see Figure 3)

Precaution: The needle guard must be held stationary while the needle is withdrawn into it.

a) Place folded sterile gauze over puncture site and hold in place with finger tip without exerting pressure.
b) Hold sides of needle guard near the front, between the index finger and thumb. Pull the hub back smoothly until the needle is completely enclosed and securely locked into the needle guard.
c) Confirm the needle is completely enclosed and securely locked into the needle guard.

23. Strip blood from donor tubing into primary container, mix and allow the tubing to refill; repeat once.

24. Seal at X marks on donor tubing to provide numbered aliquots of anticoagulated

blood for typing or crossmatching.

Note: Step 25 may be performed prior to step 23 or 24 if desired.

25. Remove and discard the Sample Diversion System and the donor needle in the

needle guard into an appropriate biohazardous waste container following established

procedures.

Component Preparation:

Notes:

• If a platelet concentrate is to be prepared, it should be separated from the red blood cells within 8 hours after blood collection.
• Fresh frozen plasma should be separated from the red blood cells and placed in the freezer at -18°C or colder within 8 hours after blood collection.
• Adsol red cell preservation solution should be added to the red blood cells immediately after the removal of plasma. Preparation of AS-1 Red Blood Cells may vary depending on processing option selected:
a) Within 8 hours of blood collection if whole blood is held at ambient temperature.
b) Within 3 days of blood collection if whole blood is refrigerated.

26. At the appropriate time, prepare the Blood-Pack unit for centrifugation by thoroughly mixing the primary container end over end, then load the unit in a centrifuge cup per the instructions on page 3.

27. Following centrifugation, remove containers from the centrifugation cup taking care not to disturb the red blood cell / plasma interface.

28. Place primary container in plasma extractor and express plasma into empty Transfer Pack container by releasing pressure plate and opening closure in tubing of primary container.

29. When desired amount of plasma has been removed, clamp tubing between Y and

plasma container.

30. Suspend Adsol red cell preservation solution container, open closure in tubing and

drain contents into primary container of CPD red blood cells. Clamp tubing.

31. Seal transfer tubing in three places between the Y-connector and primary container.

Cut middle seal being careful to avoid fluid splatter. For Double Blood-Pack unit codes, discard Adsol solution container. For other Adsol codes, the empty solution container may be used as a Transfer Pack container for further component

preparation.

32. Mix Adsol red cell preservation solution and red cells thoroughly.

33. Store suspended AS-1 Red Blood Cells between 1 and 6°C.

34. Infuse AS-1 Red Blood Cells within 42 days of collection.

Warning: Failure to achieve closed system processing conditions negates the extended storage claim and the red blood cell product must be transfused within 24 hours.

Store at Controlled Room Temperature. Protect from freezing. Avoid excessive heat.

Definition of “Controlled Room Temperature”:

“A temperature maintained thermostatically that encompasses the usual and customary working environment of 20° to 25°C (68° to 77°F); that results in a mean kinetic temperature calculated to be not more than 25°C; and that allows for excursions between 15°C and 30°C (59° and 86°F) that are experienced in pharmacies, hospitals, and warehouses. Provided the mean kinetic temperature remains in the allowed range, transient spikes up to 40°C are permitted as long as they do not exceed 24 hours ... The mean kinetic temperature is a calculated value that may be used as an isothermal storage temperature that simulates the non isothermal effects of storage temperature variations.”

Reference: United States Pharmacopeia, General Notices. United States Pharmacopeial Convention, Inc. 12601 Twinbrook Parkway, Rockville, MD.

^1 Van der Meer, P.F., & de Korte, D. “Increase of blood donation speed by optimizing the needle-totubing connection: an application of donation software.” Vox Sanguinis 2009, 97: 21-25

Sorvall is a trademark of Thermo Fisher Scientific LLC.

© 2019 Fresenius Kabi AG. All rights reserved.

PACKAGE/LABEL DISPLAY PANEL

Code 4R3464 12 Units

Fresenius Kabi

Fenwal Blood-Pack Units Quadruple

Anticoagulant Citrate Phosphate Dextrose Solution, USP (CPD); Transfer-Pack Container with Adsol Red Cell Preservation Solution

For the Collection and Processing of 500 mL Blood

Sample Diversion System, 16 ga. Ultra Thin Wall Fenwal HighFlo Needle

Rx only

Each unit consists of a primary container with 70 mL of CPD solution containing 1.84 g Sodium Citrate (dihydrate) USP, 1.78 g Dextrose (monohydrate) USP, 209 mg Citric Acid (anhydrous) USP, 155 mg Monobasic Sodium Phosphate (monohydrate) USP, pH may have been adjusted with sodium hydroxide; one 400 mL Transfer-Pack container with 110 mL of Adsol Red Cell Preservation Solution containing 2.42 g Dextrose (monohydrate) USP, 990 mg Sodium Chloride USP, 825 mg Mannitol USP, 30 mg Adenine USP; two empty 400 mL Transfer-Pack containers.

Sterile, non-pyrogenic fluid path
See instructions for use.

Single use only.

Store at Controlled Room Temperature (refer to direction insert). Protect from freezing. Avoid excessive heat.

- Open pouch by tearing across at notch.
- Direct handling of product surfaces prior to extended storage in the foil pouch, may result in mold growth.
- Unused units in open foil pouch may be kept up to 60 days by folding and securing open end of foil pouch to prevent possible loss of moisture, provided:
I) Units are not removed from foil pouch, or
II) Unused units removed from foil pouch are returned to the foil pouch within 12 hours. Units may be removed from the pouch and returned only once.
- Units removed from the foil pouch (that are not returned to the pouch within 12 hours) must be used within 4 days (96 hours). Units out of the foil pouch for longer than 96 hours must be discarded.
Manufacturer
Fresenius Kabi AG
61346 Bad Homburg / Germany
www.fresenius-kabi.com
Made in US

472815980 REV: A